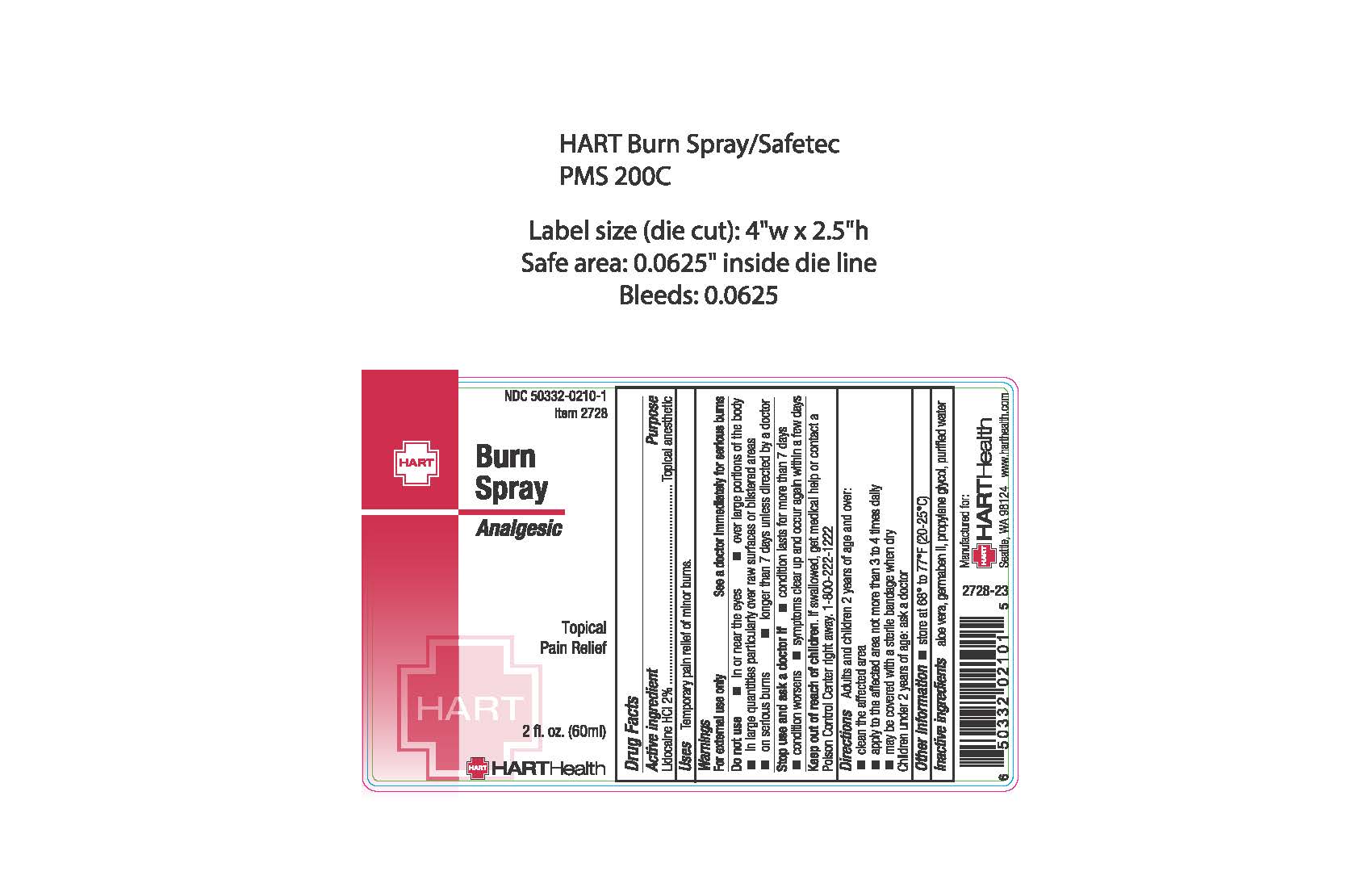 DRUG LABEL: Burn
NDC: 50332-0210 | Form: SPRAY
Manufacturer: HART Health
Category: otc | Type: HUMAN OTC DRUG LABEL
Date: 20240118

ACTIVE INGREDIENTS: LIDOCAINE HYDROCHLORIDE 2 mg/100 mL
INACTIVE INGREDIENTS: ALOE VERA WHOLE; DIAZOLIDINYL UREA; PROPYLENE GLYCOL; WATER

Burn Spray

Active Ingredients:

Lidocaine HCL 2%

Purpose:

Topical Anesthetic

Uses:

Temporary pain relief of minor burns

Warnings

For external use only

See a doctor immediately or serious burns

Do not use

- in or near the eyes
- over large portions of the body
- in large quantities particularly over raw surfaces or blistered areas
- on serious burns
- longer than 7 days unless directed by a doctor

Stop use and ask a doctor if

- condition worsens
- condition lasts for more than 7 days
- symptoms clear up and occur again within a few days

Keep out of reach of children.

If swallowed, get medical help or contact a Poison Control Center right away. 1-800-222-1222

Directions:

Adults and children 12 years of age and over:

- clean the affected area
- apply to the affected area not more than 3 to 4 times dailys
- may be covered with a sterile bandage when dry

Children under 12 years of age: ask a doctor

OTHER SAFETY INFORMATION

store at 68° to 77°F (20-25°C)

Inactive Ingredients

aloe vera, germaben II, propylene glycol, purified water